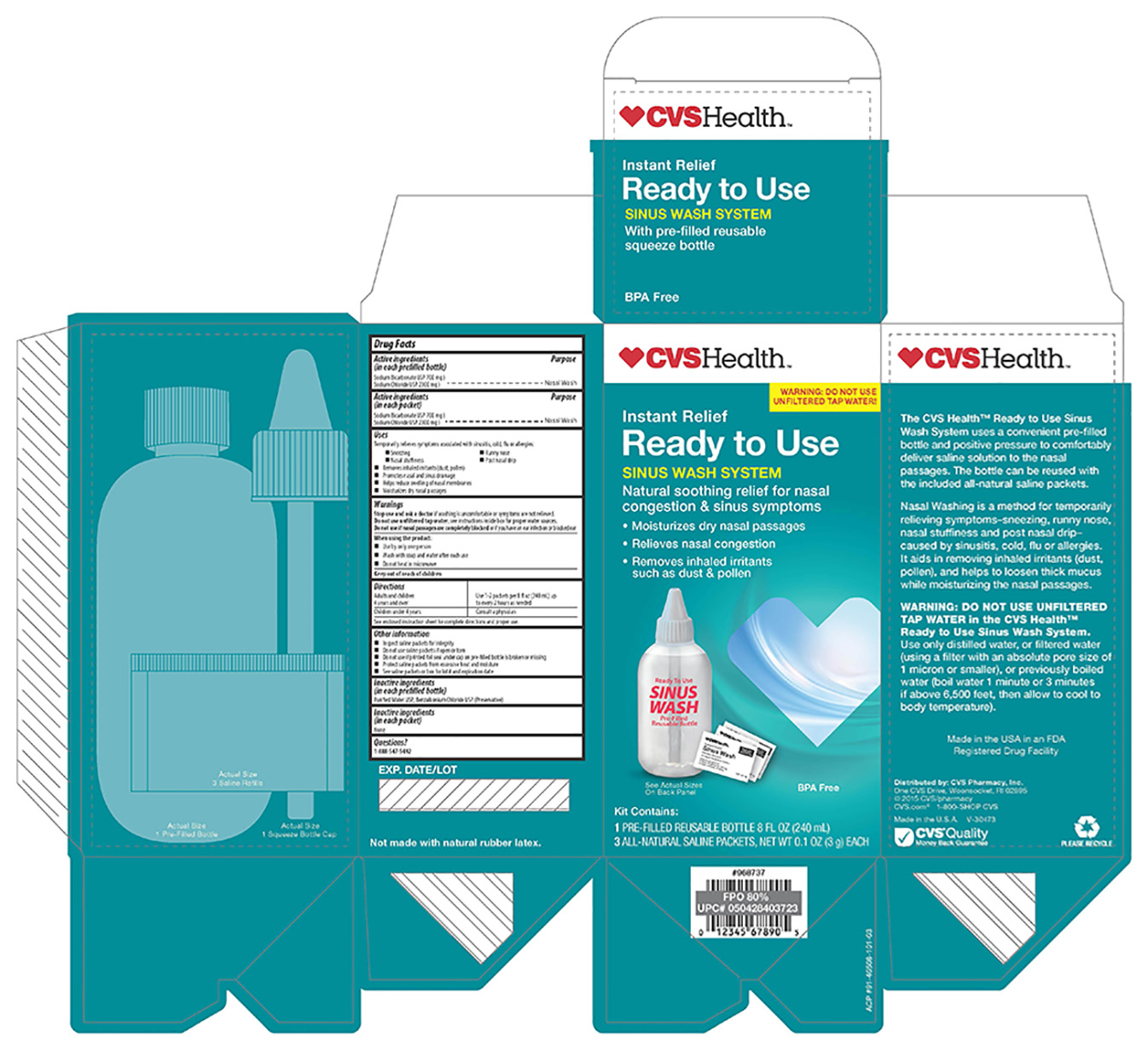 DRUG LABEL: CVS
NDC: 59779-867 | Form: KIT | Route: NASAL
Manufacturer: CVS Pharmacy
Category: otc | Type: HUMAN OTC DRUG LABEL
Date: 20160325

ACTIVE INGREDIENTS: SODIUM BICARBONATE 22.2 mg/.1 g; SODIUM CHLORIDE 77.8 mg/.1 g; SODIUM BICARBONATE 22.8 mg/100 mg; SODIUM CHLORIDE 77.8 mg/100 mg
INACTIVE INGREDIENTS: WATER; BENZALKONIUM CHLORIDE; WATER

Active ingredients

(in each prefilled bottle)

Sodium Bicarbonate USP 700 mg }

Sodium Chloride USP 2300 mg }

Active ingredients

(in each packet)

Sodium Bicarbonate USP 700 mg }

Sodium Chloride USP 2300 mg }

Purpose

Nasal Wash

Purpose

Nasal Wash

Uses

Temporarily relieves symptoms associated with sinusitis, cold, flue or allergies:

-sneezing

-Runny nose

-Nasal stuffiness

-Post nasal drip

-Removes inhaled irritants (dust, pollen)

-Promotes nasal and sinus drainage

-Helps reduce swelling of nasal membranes

-Moisturizes dry nasal passages

Warnings

Stop use and ask a doctor if washing is uncomfortable or symptoms are not relieved.

Do not use unfiltered tap water. see instructions inside box for proper water sources.

Do not use if nasal passages are completely blocked or if you have an ear infection or blocked ear.

When using this product:

-Use by only one person

-Wash with soap and water after each use

-Do not heat in microwave

Keep out of reach of children

Directions

Adults and children 4 years and over: Use 1 - 2 packets per 8 fl oz (240 mL) up to every 2 hours as needed

Children under 4 years: Consult a physician

See enclosed instruction sheet for complete directions and proper use.

Other information

- inspect saline packets for integrity
- Do not use saline packets if open or torn
- Do not use if printed foil seal under cap on pre-filled bottle is broken or missing
- Protect saline packets from excessive heat and moisture
- See saline packets or box for lot number and expiration date

Inactive ingredients

(in each prefilled bottle)

Purified Water USP, Benzalkonium Chloride USP (Preservative)

Inactive ingredient

(in each packet)

none

Questions?

1-888-547-5492

INSTRUCTIONS FOR USE

Sinus Wash
Pre-Filled Ready to Use
Saline Sinus Wash Kit
Instructions
DO NOT
SINUS WASH
WITH UNFILTERED
TAP WATER.
See important note*
for proper water
sources.
Read through entire instruction sheet
before using for the fi rst time.
* IMPORTANT NOTE
Do not sinus wash with unfi ltered tap water. Use either distilled, or
sterile, or fi ltered (using a fi lter with an absolute pore size of 1 micron or
smaller) or previously boiled water (boil water 1 minute or 3 minutes if at
elevations above 6,500 feet, then allow to cool to body temperature).
Instructions for Use of the Ready to Use
Sinus Wash Kit (pre-filled with solution)
Read through entire section.
1. Wash your hands and remove cap and foil safety seal from the top of
the pre-filled bottle.
2. Assemble white cap and tube and then place on pre-filled bottle and
tighten securely.
3. Lean over the sink with your head bent down so you are looking directly
into the basin. Place the tip of the cap up to the right nostril and gently
insert the tip so that it forms a comfortable seal. Aim the tip at the back
of your head, not at the top of your head.
4. Squeeze the bottle gently so that the solution enters the right nostril. Do not
inhale or “snort” the solution into the nose – breathe through your mouth.
5. In a few moments, the solution will begin to drain out of the left
nostril. Continue to squeeze the bottle gently until you have used
approximately half of the solution.
6. Remove the tip of the bottle from your nostril, then exhale through both
nostrils to clear them of excess mucus and solution. Gently blow your
nose into a tissue.
7. Repeat the procedure on the left nostril with the remaining solution.
8. A small amount of solution will remain at the bottom of the bottle.
Discard the remaining solution.
9. Thoroughly rinse the bottle after each use with water that has been
either distilled, sterilized, filtered or previously boiled and leave the
bottle open to air dry completely.
10. Bottle, tube and cap may be reused with included packets. See
instructions that follow.
Isotonic Solution
Hypertonic Solution
1 Saline Packet per
8 fl oz. (240 mL)
2 Saline Packets per
8 fl oz. (240 mL)
Refill instructions for the Ready to Use
Sinus Wash Kit (with saline packets)
Read through entire section.
The Ready to Use Sinus Wash Kit can be used with the enclosed Saline
packets to make either an Isotonic or Hypertonic solution. Check with the
guide below or consult with your physician for best use.
An Isotonic solution creates a mild, less concentrated salt solution of 9 mg
of Sodium Chloride per mL of water, which has a similar salt concentration
of your body and may be more comfortable to use for some people initially
than a more concentrated Hypertonic solution.
A Hypertonic solution creates a higher, more concentrated salt solution
which is similar to the salt content of ocean water.
1. Wash your hands and make sure the bottle has been rinsed with water
that has been either distilled, sterilized, filtered or previously boiled.
2. Pour the pre-mixed saline dry ingredients into the Squeeze Bottle.
First-time users should start with 1 packet of the saline dry ingredients
to make an isotonic solution. As you become more accustomed to
the system, work up to using 2 full packets for a hypertonic solution.
Additional packets may be purchased from your nearest pharmacy.
3. Fill the bottle to the 8 oz line with proper water*.
4. Tighten the cap on the bottle securely, place one finger over the tip
of the cap and gently shake the bottle until the dry ingredients have
completely dissolved.
5. Lean over the sink with your head bent down so you are looking directly
into the basin. Place the tip of the cap up to the right nostril and gently
insert the tip so that it forms a comfortable seal. Aim the tip at the back
of your head, not at the top of your head. (continued on back)
Hints for a more comfortable nasal wash:
• Begin using the Sinus Wash System slowly – especially with children. A full
pot or bottle of solution on each side is not necessary to receive the full benefit.
• If the solution is too warm or too cold, the nasal wash will be uncomfortable.
• If stinging or irritation occurs, try using 1 packet of dry ingredients per
pot or bottle. Gradually work up to using the solution at full strength using 2
full packets per bottle. Do not use less than 1 packet.
• If you experience ear discomfort after use, try to blow your nose more gently
after the wash. If the problem persists, the openings of your Eustachian tubes
may be particularly wide and use of the system should be discontinued.
• Breathe continuously through the mouth when using the Sinus Wash System
to avoid solution draining from the back of the nose into the mouth.
• Some people experience irritation of the skin just inside the nostrils with
repeated nasal washing. Applying a thin layer of aloe to the inside of the
nostrils before or after the nasal wash will be soothing